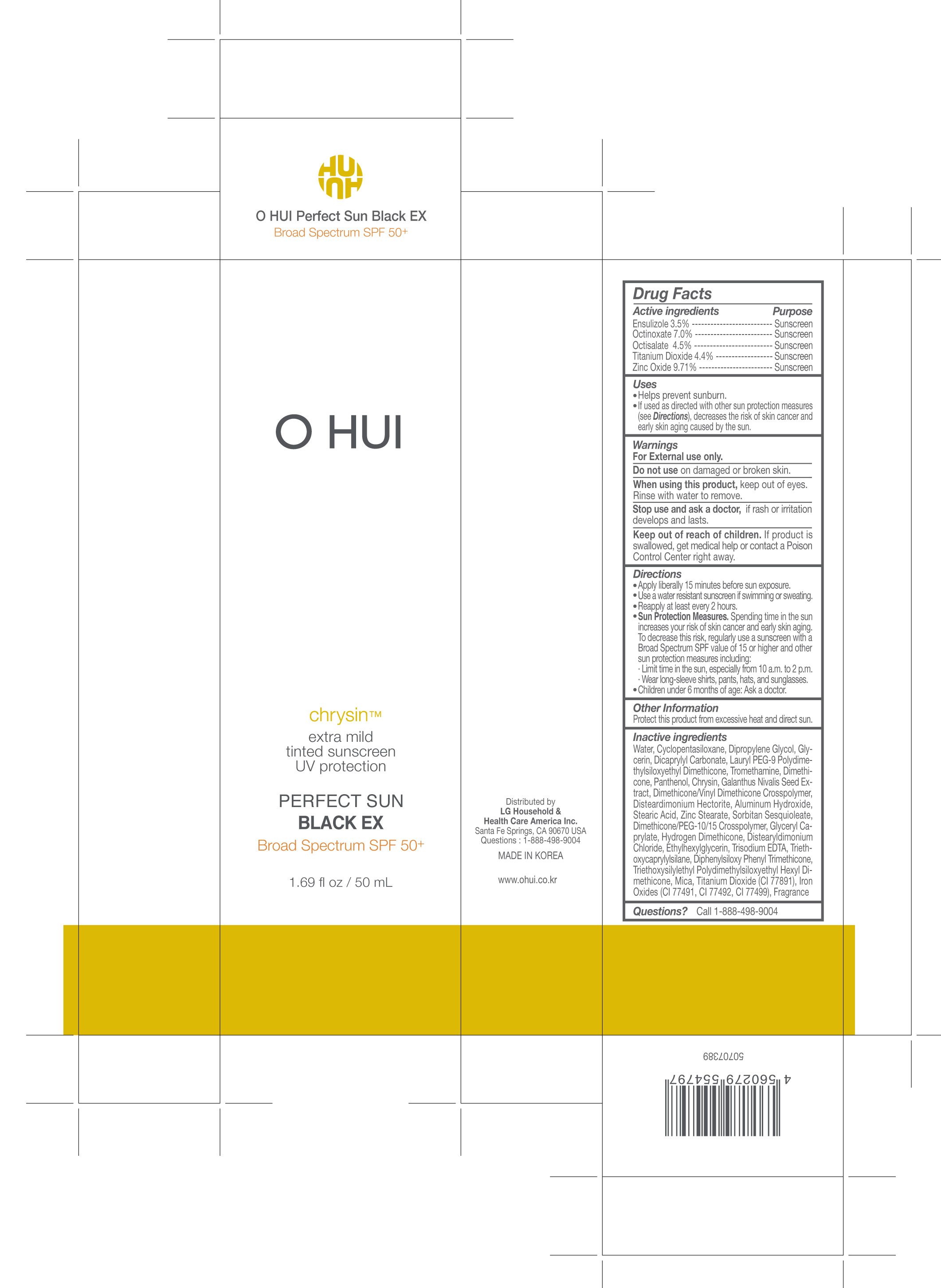 DRUG LABEL: O HUI Perfect Sun Black EX Broad Spectrum SPF 50
NDC: 53208-604 | Form: CREAM
Manufacturer: LG Household and Health Care Inc
Category: otc | Type: HUMAN OTC DRUG LABEL
Date: 20170601

ACTIVE INGREDIENTS: TITANIUM DIOXIDE 2.2 g/50 g; ENSULIZOLE 1.75 g/50 g; OCTINOXATE 3.5 g/50 g; OCTISALATE 2.25 g/50 g; ZINC OXIDE 4.86 g/50 g
INACTIVE INGREDIENTS: DISTEARDIMONIUM HECTORITE; WATER; DIPROPYLENE GLYCOL; TROMETHAMINE; STEARIC ACID; ALUMINUM HYDROXIDE; SORBITAN SESQUIOLEATE; DIMETHICONE/VINYL DIMETHICONE CROSSPOLYMER (SOFT PARTICLE); PHENYL TRIMETHICONE; DISTEARYLDIMONIUM CHLORIDE; TRIETHOXYCAPRYLYLSILANE; TRIETHYLHEXANOIN; PHENOXYETHANOL; LAURYL PEG-9 POLYDIMETHYLSILOXYETHYL DIMETHICONE; CHRYSIN; HYDROGEN DIMETHICONE (20 CST); DIMETHICONE; GLYCERIN; DICAPRYLYL CARBONATE; PANTHENOL; GALANTHUS NIVALIS SEED; GLYCERYL CAPRYLATE; DISTEARYLDIMONIUM; ETHYLHEXYLGLYCERIN; DIPHENYLSILOXY PHENYL TRIMETHICONE; MICA

ACTIVE INGREDIENTS

ENSULIZOLE 3.5%, OCTINOXATE 7.0%, OCTISALATE 4.5%, TITANIUM DIOXIDE 4.4%, ZINC OXIDE 9.71%

PURPOSE

Sunscreen

USES

- Helps prevent sunburn.
- If used as directed with other sun protection measures (see Directions), may decrease the risk of skin cancer and early skin aging caused by the sun.

WARNINGS

For external use only

Do not use on damaged or broken skin.

When using this product: Keep out of the eyes. Rinse with water to remove.

Stop use and ask doctor, if rash occurs.

Keep out of reach of children. If product is swallowed, get medical help or

contact a Posion Control Center right away.

DIRECTIONS

- Apply liberally 15 minutes before sun exposure.
- Use a water resistant sunscreen if swimming or sweating.
- Reapply at least every 2 hours.
- Sun Protection Measures. Spending time in the sun increases your risk of skin cancer and early skin aging. To decrease this risk, regularly use a sunscreen with a Broad Spectrum SPF value of 15 or higher and othersun protection measures including:

- Limit time in the sun, especially from 10 a.m. to 2 p.m.

- Wear longsleeved shirts, pants, hats, and sunglasses.

- Children under 6 months: Ask a doctor.

OTHER INFORMATION

- Protect the product in this container from excessive heat and direct sun.

INACTIVE INGREDIENTS

WATER, CYCLOPENTASILOXANE, DIPROPYLENE GLYCOL, GLYCERIN, DICAPRYLYL CARBONATE, LAURYL PEG-9 POLYDIMETHYLSILOXYETHYL DIMETHICONE, TROMETHAMINE, DIMETHICONE, PANTHENOL, CHRYSIN, GALANTHUS NIVALIS SEED EXTRACT, DIMETHICONE/VINYL DIMETHICONE CROSSPOLYMER, DISTEARDIMONIUM HECTORITE, ALUMINUM HYDROXIDE, STEARIC ACID, ZINC STEARATE, SORBITAN SESQUIOLEATE, DIMETHICONE/PEG-10/15 CROSSPOLYMER, GLYCERYL CAPRYLATE, HYDROGEN DIMETHICONE, DISTEARYLDIMONIUM CHLORIDE, ETHYLHEXYLGLYCERIN, TRISODIUM EDTA, TRIETHOXYCAPRYLYLSILANE, DIPHENYLSILOXY PHENYL TRIMETHICONE, TRIETHOXYSILYLETHYL POLYDIMETHYLSILOXYETHYL HEXYL DIMETHICONE, MICA, TITANIUM DIOXIDE (CI 77891), IRON OXIDES (CI 77491, CI 77492, CI 77499), FRAGRANCE

PRINCIPAL DISPLAY PANEL

O HUI Perfect Sun Black EX

Sunscreen Broad Spectrum SPF 50+

1.69 fl oz / 50 ml